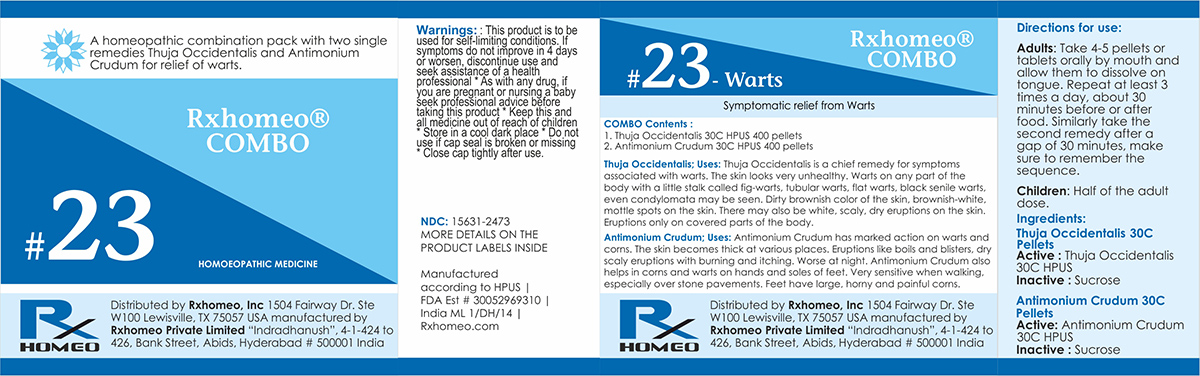 DRUG LABEL: Rxhomeo Homeopathic Combo 23
NDC: 15631-2473 | Form: KIT | Route: ORAL
Manufacturer: Rxhomeo Private Limited d.b.a.
Category: homeopathic | Type: HUMAN OTC DRUG LABEL
Date: 20161024

ACTIVE INGREDIENTS: THUJA OCCIDENTALIS LEAFY TWIG 1 [hp_X]/1 1; ANTIMONY TRISULFIDE 3 [hp_X]/1 1
INACTIVE INGREDIENTS: SUCROSE; LACTOSE

ACTIVE INGREDIENT

THUJA OCCIDENTALIS HPUS 1X and higher

ANTIMONIUM CRUDUM HPUS 3X and higher

USES

A homeopathic combination pack with two single remedies Thuja Occidentalis and Antimonium Crudum for relief of warts.

Thuja Occidentalis: Thuja Occidentalis is a chief remedy for symptoms associated with warts. The skin looks very unhealthy. Warts on any part of the body with a little stalk called fig-warts, tubular warts, flat warts, black senile warts, even condylomata may be seen. Dirty brownish color of the skin, brownish-white, mottle spots on the skin. There may also be white, scaly, dry eruptions on the skin. Eruptions only on covered parts of the body.

Antimonium Crudum: Antimonium Crudum has marked action on warts and corns. The skin becomes thick at various places. Eruptions like boils and blisters, dry scaly eruptions with burning and itching. Worse at night. Antimonium Crudum also helps in corns and warts on hands and soles of feet. Very sensitive when walking, especially over stone pavements. Feet have large, horny and painful corns.

INDICATIONS

Condition listed above or as directed by the physician

DOSAGE

Adults: Take 4-5 pellets or tablets orally by mouth and allow them to dissolve on tongue. Repeat at least 3 times a day, about 30 minutes before or after food. Similarly take the second remedy after a gap of 30 minutes, make sure to remember the sequence.

Children: Half of the adult dose.

WARNINGS

This product is to be used for self-limiting conditions

STOP USE

If symptoms do not improve in 4 days, or worsen, discontinue use and seek assistance of health professional

KEEP OUT OF REACH OF CHILDREN

Keep this and all medication out of reach of children

Do not use if capseal is broken or missing.

Close the cap tightly after use.

INACTIVE INGREDIENTS

Sucrose for Pellets.

Lactose for Tablets.

STORAGE

Store in a cool dark place

QUESTIONS OR COMMENTS

www.Rxhomeo.com | 1.888.2796642 | info@rxhomeo.com
Rxhomeo, Inc 1504 Fairway Dr. Ste W 100 Lewisville, TX 75057 USA